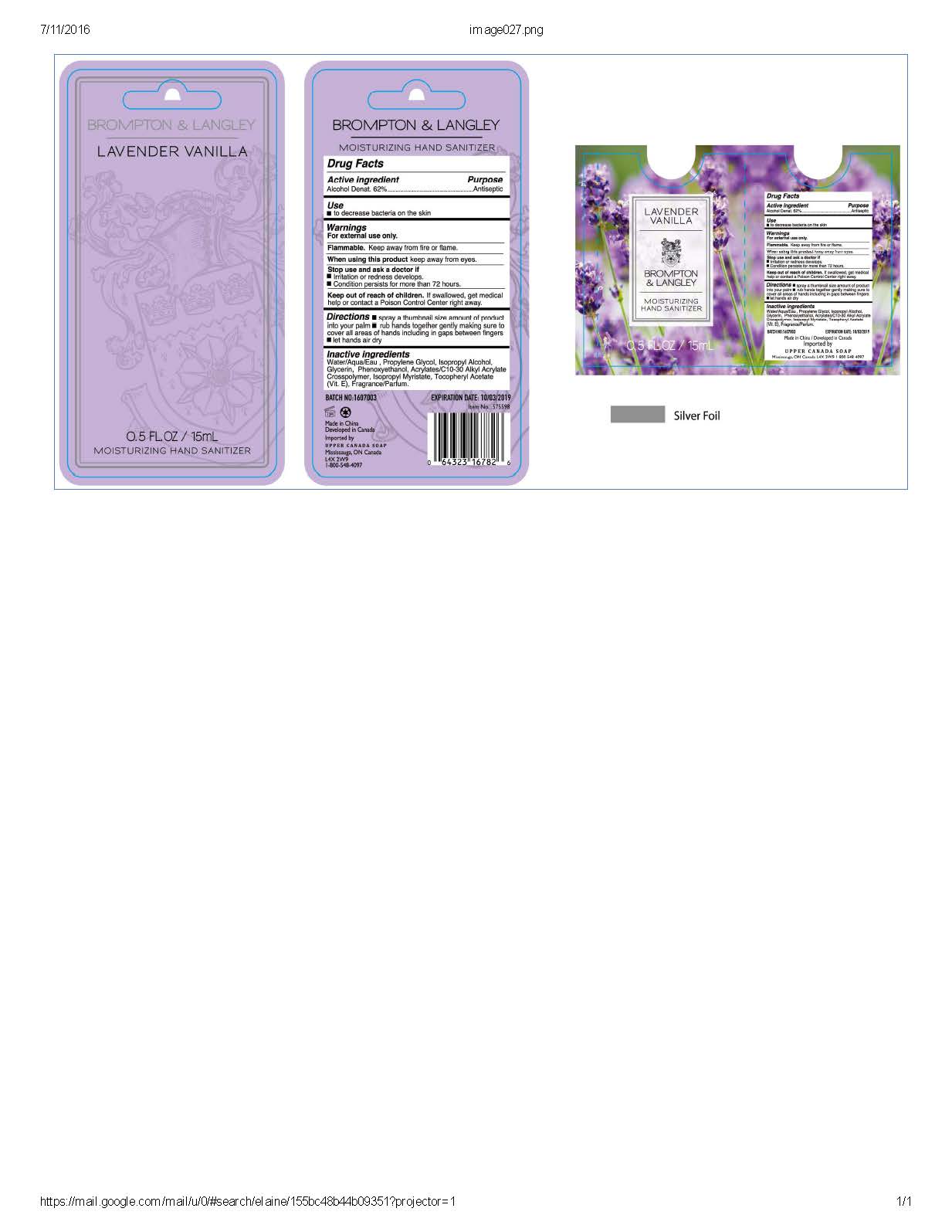 DRUG LABEL: Brompton and Langley Lavender Vanilla Hand Sanitizer
NDC: 70805-006 | Form: GEL
Manufacturer: Cita International Limited
Category: otc | Type: HUMAN OTC DRUG LABEL
Date: 20160713

ACTIVE INGREDIENTS: ALCOHOL 0.26 g/26 g
INACTIVE INGREDIENTS: CARBOMER INTERPOLYMER TYPE A (55000 CPS); WATER; GLYCERIN; PROPYLENE GLYCOL; ISOPROPYL ALCOHOL; PHENOXYETHANOL; METHOXY PEG-40; ISOPROPYL MYRISTATE; .ALPHA.-TOCOPHEROL ACETATE

Active Ingredient

Alcohol 62%

Purpose: Antiseptic

Use

To decrease bacteria on the skin that could cause disease.

Keep out of reach of children.

Warnings

- Keep away from flame or fire
- for external use only-hands.
- keep out of eyes.
- stop use and ask a Doctor if irritation or redness persists for more than 72 hours
- do not inhale or ingest. if swallowed, get medical help or contact a poison control center right away.

Directions

- spray a thumb size amount into hands.
- rub hands together gently making sure to cover all areas in between fingers
- let hands air dry

Inactive Ingredients

water (aqua/eau), glycerin, propylen glycol, Isopropyl alcohol, phenoxythenol, acrylates,

lauryl glycol ether, carbomer, Vitamin E, fragrance (parfum).

INDICATIONS AND USAGE

Brompton and Langley
Lavender Vanilla Scentend Hand Sanitizer
15mL